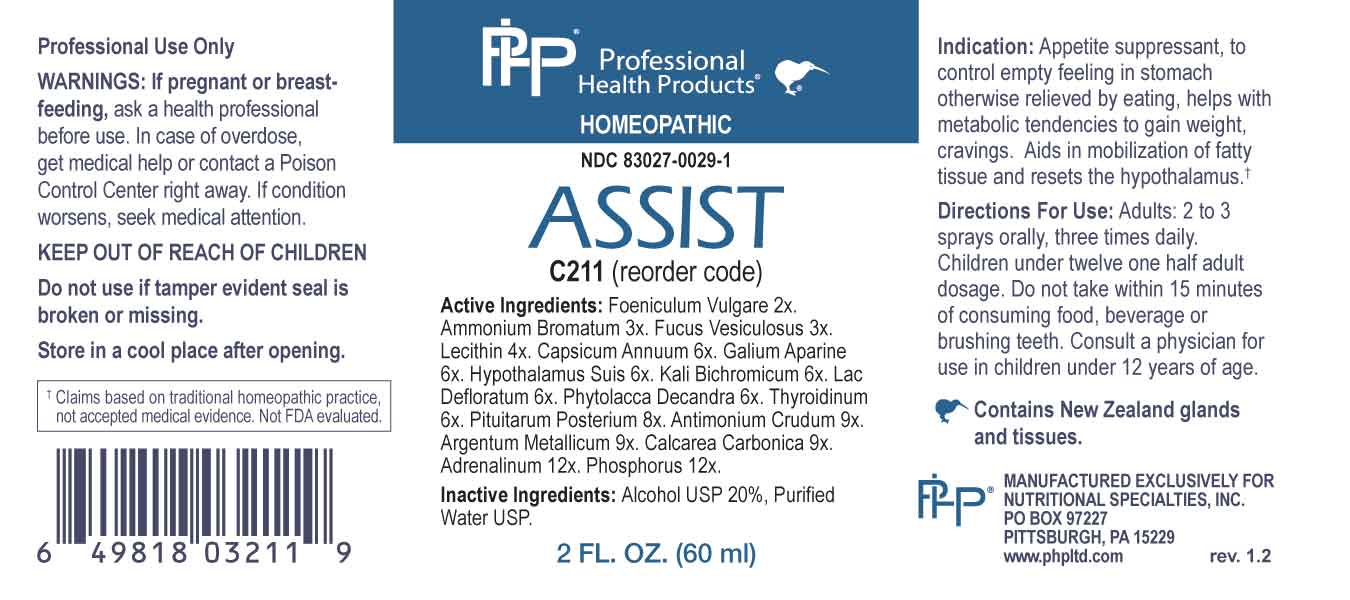 DRUG LABEL: Assist
NDC: 83027-0029 | Form: SPRAY
Manufacturer: Nutritional Specialties, Inc.
Category: homeopathic | Type: HUMAN OTC DRUG LABEL
Date: 20240724

ACTIVE INGREDIENTS: FOENICULUM VULGARE FRUIT 2 [hp_X]/1 mL; AMMONIUM BROMIDE 3 [hp_X]/1 mL; FUCUS VESICULOSUS 3 [hp_X]/1 mL; EGG PHOSPHOLIPIDS 4 [hp_X]/1 mL; CAPSICUM 6 [hp_X]/1 mL; GALIUM APARINE WHOLE 6 [hp_X]/1 mL; SUS SCROFA PITUITARY GLAND 6 [hp_X]/1 mL; POTASSIUM DICHROMATE 6 [hp_X]/1 mL; SKIM MILK 6 [hp_X]/1 mL; PHYTOLACCA AMERICANA ROOT 6 [hp_X]/1 mL; THYROID, BOVINE 6 [hp_X]/1 mL; BOS TAURUS PITUITARY GLAND, POSTERIOR 8 [hp_X]/1 mL; ANTIMONY TRISULFIDE 9 [hp_X]/1 mL; SILVER 9 [hp_X]/1 mL; OYSTER SHELL CALCIUM CARBONATE, CRUDE 9 [hp_X]/1 mL; EPINEPHRINE 12 [hp_X]/1 mL; PHOSPHORUS 12 [hp_X]/1 mL
INACTIVE INGREDIENTS: WATER; ALCOHOL

DRUG FACTS:

ACTIVE INGREDIENTS:

Foeniculum Vulgare 2X, Ammonium Bromatum 3X, Fucus Vesiculosus 3X, Lecithin 4X, Capsicum Annuum 6X, Galium Aparine 6X, Hypothalamus Suis 6X, Kali Bichromicum 6X, Lac Defloratum 6X, Phytolacca Decandra 6X, Thyroidinum 6X, Pituitarum Posterium 8X, Antimonium Crudum 9X, Argentum Metallicum 9X, Calcarea Carbonica 9X, Adrenalinum 12X, Phosphorus 12X.

PURPOSE:

Appetite suppressant, to control empty feeling in stomach otherwise relieved by eating, helps with metabolic tendencies to gain weight, cravings. Aids in mobilization of fatty tissue and resets the hypothalamus.†

†Claims based on traditional homeopathic practice, not accepted medical evidence. Not FDA evaluated.

WARNINGS:

Professional Use Only

If pregnant or breast-feeding, ask a health professional before use.

In case of overdose, get medical help or contact a Poison Control Center right away.

If condition worsens, seek medical attention.

KEEP OUT OF REACH OF CHILDREN

Do not use if tamper evident seal is broken or missing.

Store in a cool place after opening

KEEP OUT OF REACH OF CHILDREN:

In case of overdose, get medical help or contact a Poison Control Center right away.

DIRECTIONS:

Adults: 2 to 3 sprays orally, three times daily. Children under twelve one half adult dosage. Do not take within 15 minutes of consuming food, beverage or brushing teeth. Consult a physician for use in children under 12 years of age.

INDICATIONS:

Appetite suppressant, to control empty feeling in stomach otherwise relieved by eating, helps with metabolic tendencies to gain weight, cravings. Aids in mobilization of fatty tissue and resets the hypothalamus.†

†Claims based on traditional homeopathic practice, not accepted medical evidence. Not FDA evaluated.

INACTIVE INGREDIENTS:

Alcohol USP 20%, Purified Water USP.

QUESTIONS:

MANUFACTURED EXCLUSIVELY FOR

NUTRITIONAL SPECIALTIES, INC.

PO BOX 97227

PITTSBURG, PA 15229

www.phpltd.com

PACKAGE LABEL DISPLAY:

Professional

Health Products

HOMEOPATHIC

NDC 83027-0029-1

ASSIST

2 FL. OZ (60 ml)